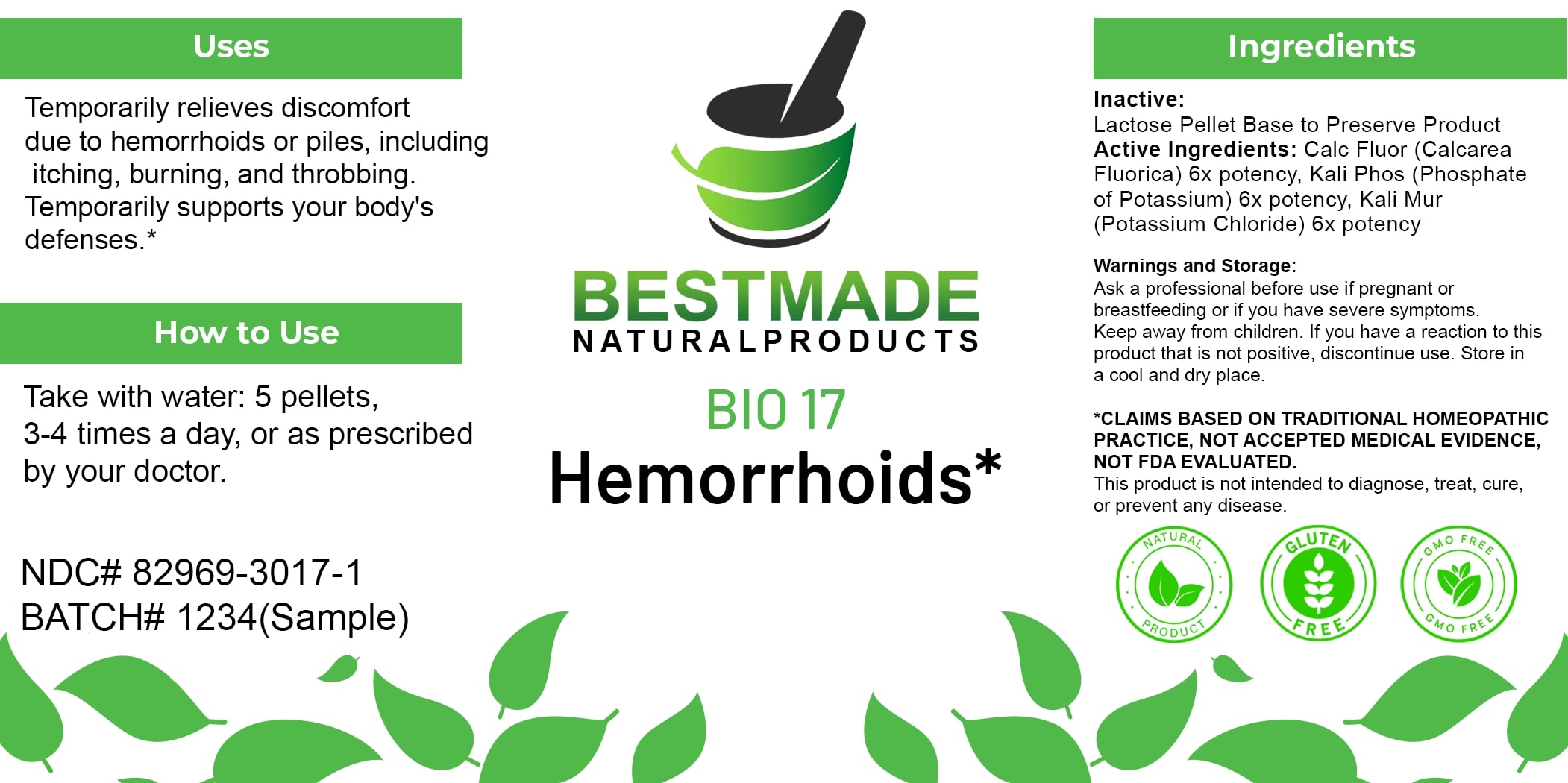 DRUG LABEL: Bestmade Natural Products Bio17
NDC: 82969-3017 | Form: TABLET, SOLUBLE
Manufacturer: Bestmade Natural Products
Category: homeopathic | Type: HUMAN OTC DRUG LABEL
Date: 20250122

ACTIVE INGREDIENTS: CALCIUM FLUORIDE 6 [hp_X]/6 [hp_X]; POTASSIUM PHOSPHATE, UNSPECIFIED FORM 6 [hp_X]/6 [hp_X]; FERRIC PYROPHOSPHATE 6 [hp_X]/6 [hp_X]; POTASSIUM CHLORIDE 6 [hp_X]/6 [hp_X]
INACTIVE INGREDIENTS: LACTOSE, UNSPECIFIED FORM 6 [hp_X]/6 [hp_X]

BIO17

DOSAGE AND ADMINISTRATION

How to Use

Take with water: 5 pellets, 3-4 times a day, or as prescribed by your doctor.

Uses

Temporarily relieves discomfort due to hemorrhoids or piles, including itching, burning, and throbbing. Temporarily supports your body's defenses.*

*CLAIMS BASED ON TRADITIONAL HOMEOPATHIC PRACTICE, NOT ACCEPTED MEDICAL EVIDENCE. NOT FDA EVALUATED.

This product is not intended to diagnose, treat, cure, or prevent any disease.

Uses

Temporarily relieves discomfort due to hemorrhoids or piles, including itching, burning, and throbbing. Temporarily supports your body's defenses.*

*CLAIMS BASED ON TRADITIONAL HOMEOPATHIC PRACTICE, NOT ACCEPTED MEDICAL EVIDENCE. NOT FDA EVALUATED.

This product is not intended to diagnose, treat, cure, or prevent any disease.

INACTIVE INGREDIENT

Ingredients

Inactive: Lactose Pellet Base to Preserve Product

ACTIVE INGREDIENT

Active Ingredients: Calc Fluor (Calcarea Fluorica) 6x potency, Kali Phos (Phosphate of Potassium) 6x potency, Kali Mur (Potassium Chloride) 6x potency

KEEP OUT OF REACH OF CHILDREN

Warnings and Storage:

Ask a professional before use if pregnant or breastfeeding or if you have severe symptoms. Keep away from children. If you have a reaction to this product that is not positive, discontinue use. Store in a cool and dry place.

Warnings and Storage:

Ask a professional before use if pregnant or breastfeeding or if you have severe symptoms. Keep away from children. If you have a reaction to this product that is not positive, discontinue use. Store in a cool and dry place.

*CLAIMS BASED ON TRADITIONAL HOMEOPATHIC PRACTICE, NOT ACCEPTED MEDICAL EVIDENCE. NOT FDA EVALUATED.

This product is not intended to diagnose, treat, cure, or prevent any disease.

Entire package label